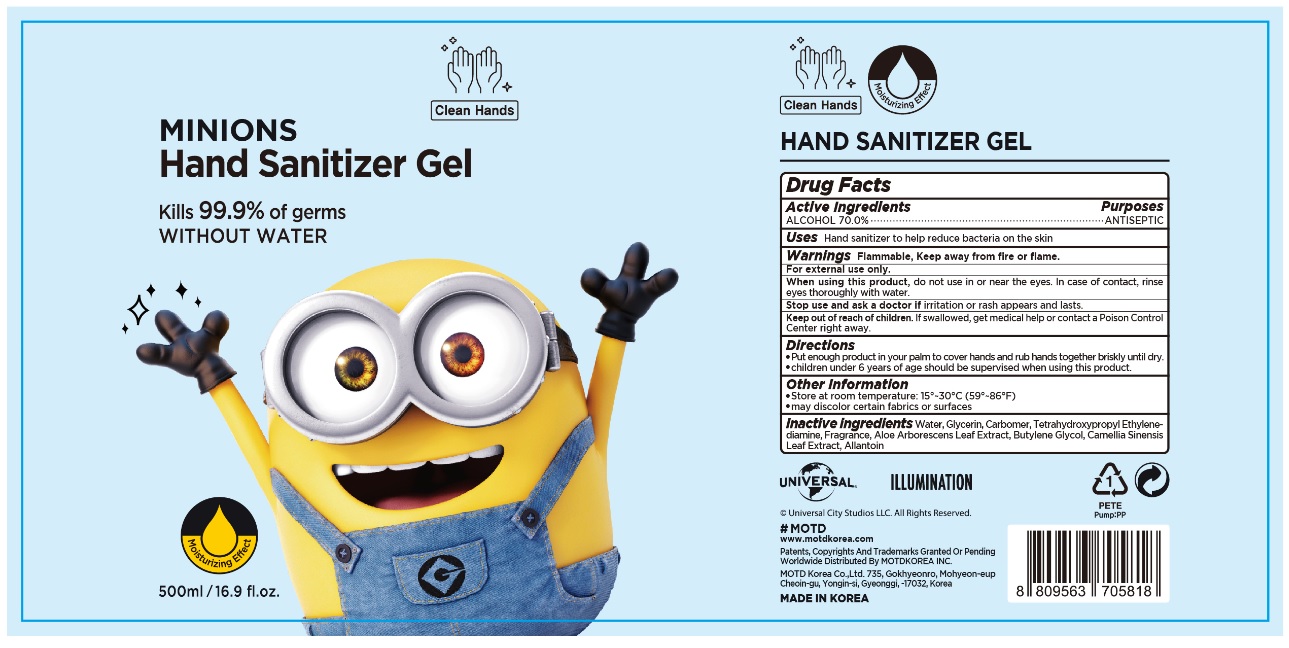 DRUG LABEL: MINIONS Hand Sanitizer Gel
NDC: 74004-701 | Form: GEL
Manufacturer: Ester Co., Ltd.
Category: otc | Type: HUMAN OTC DRUG LABEL
Date: 20200521

ACTIVE INGREDIENTS: ALCOHOL 350 mL/500 mL
INACTIVE INGREDIENTS: ALLANTOIN; GREEN TEA LEAF; BUTYLENE GLYCOL; EDETOL; CARBOMER HOMOPOLYMER, UNSPECIFIED TYPE; WATER; ALOE ARBORESCENS LEAF; GLYCERIN

[Ester Co., Ltd.-MINIONS HAND SANITIZER GEL] 500 ml : BOTTLE+PUMP : 74004-701-01